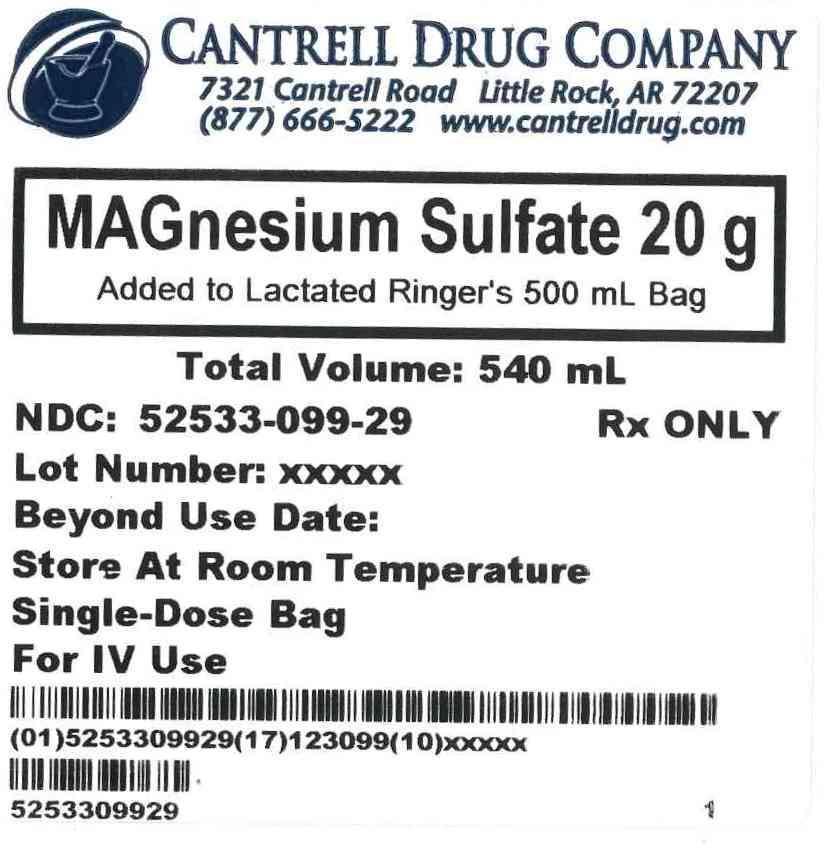 DRUG LABEL: Magnesium Sulfate
NDC: 52533-099 | Form: INJECTION, SOLUTION
Manufacturer: Cantrell Drug Company
Category: prescription | Type: HUMAN PRESCRIPTION DRUG LABEL
Date: 20121121

ACTIVE INGREDIENTS: MAGNESIUM SULFATE 20 g/500 mL
INACTIVE INGREDIENTS: WATER; SODIUM CHLORIDE 3 g/500 mL; SODIUM LACTATE 1.55 g/500 mL; POTASSIUM CHLORIDE 0.15 g/500 mL; CALCIUM CHLORIDE 0.1 g/500 mL

Magnesium Sulfate 20 g Added to Lactated Ringer's 500 mL Bag